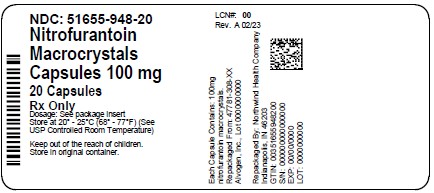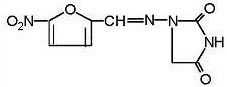 DRUG LABEL: nitrofurantoin macrocrystals
NDC: 51655-948 | Form: CAPSULE
Manufacturer: Northwind Health Company, LLC
Category: prescription | Type: HUMAN PRESCRIPTION DRUG LABEL
Date: 20260101

ACTIVE INGREDIENTS: NITROFURANTOIN 100 mg/1 1
INACTIVE INGREDIENTS: STARCH, CORN; D&C YELLOW NO. 10; FD&C YELLOW NO. 6; GELATIN, UNSPECIFIED; LACTOSE, UNSPECIFIED FORM; TALC; TITANIUM DIOXIDE

Nitrofurantoin Capsules, USP (macrocrystals)

To reduce the development of drug-resistant bacteria and maintain the effectiveness of nitrofurantoin capsules (macrocrystals) and other antibacterial drugs, nitrofurantoin capsules (macrocrystals) should be used only to treat or prevent infections that are proven or strongly suspected to be caused by bacteria.

DESCRIPTION

Nitrofurantoin (macrocrystals) is a synthetic chemical of controlled crystal size. It is a stable, yellow, crystalline compound. Nitrofurantoin capsules, USP (macrocrystals) are an antibacterial agent for specific urinary tract infections. It is available in 25 mg, 50 mg, and 100 mg capsules for oral administration.

1-[[(5-nitro-2-furanyl)methylene] amino]-2,4-imidazolidinedione

Inactive Ingredients: Each capsule contains edible black ink, gelatin, lactose, starch, talc, titanium dioxide, and may contain FD&C Yellow No. 6 and D&C Yellow No. 10.

CLINICAL PHARMACOLOGY

Nitrofurantoin (macrocrystals) is a larger crystal form of nitrofurantoin. The absorption of nitrofurantoin (macrocrystals) is slower and its excretion somewhat less when compared to nitrofurantoin. Blood concentrations at therapeutic dosage are usually low. It is highly soluble in urine, to which it may impart a brown color.

Following a dose regimen of 100 mg q.i.d. for 7 days, average urinary drug recoveries (0 to 24 hours) on day 1 and day 7 were 37.9% and 35.0%.

Unlike many drugs, the presence of food or agents delaying gastric emptying can increase the bioavailability of nitrofurantoin capsules (macrocrystals), presumably by allowing better dissolution in gastric juices.

MICROBIOLOGY

Nitrofurantoin is a nitrofuran antimicrobial agent with activity against certain Gram-positive and Gram-negative bacteria.

Mechanism of Action

The mechanism of the antimicrobial action of nitrofurantoin is unusual among antibacterials.

Nitrofurantoin is reduced by bacterial flavoproteins to reactive intermediates which inactivate or alter bacterial ribosomal proteins and other acromolecules. As a result of such inactivations, the vital biochemical processes of protein synthesis, aerobic energy metabolism, DNA synthesis, RNA synthesis, and cell wall synthesis are inhibited. Nitrofurantoin is bactericidal in urine at therapeutic doses. The broad-based nature of this mode of action may explain the lack of acquired bacterial resistance to nitrofurantoin, as the necessary multiple and simultaneous mutations of the target macromolecules would likely be lethal to the bacteria.

Interactions with Other Antibiotics

Antagonism has been demonstrated in vitrobetween nitrofurantoin and quinolone antimicrobials. The clinical significance of this finding is unknown.

Development of resistance to nitrofurantoin has not been a significant problem since its introduction in 1953. Cross-resistance with antibiotics and sulfonamides has not been observed, and transferable resistance is, at most, a very rare phenomenon.

Nitrofurantoin has been shown to be active against most strains of the following bacteria both in vitroand in clinical infections (see INDICATIONS AND USAGE):

Aerobic and facultative Gram-positive microorganisms:

Staphylococcus aureus

Enterococci (e.g. Enterococcus faecalis)

Aerobic and facultative Gram-negative microorganisms:

Escherichia coli

NOTE:While nitrofurantoin has excellent activity against Enterococcus faecalis, the majority of Enterococcus faeciumisolates are not susceptible to nitrofurantoin.

At least 90 percent of the following microorganisms exhibit an in vitrominimum inhibitory concentration (MIC) less than or equal to the susceptible breakpoint for nitrofurantoin. However, the efficacy of nitrofurantoin in treating clinical infections due to these microorganisms has not been established in adequate and well-controlled trials.

Aerobic and facultative Gram-positive microorganisms:

Coagulase-negative staphylococci (including Staphylococcus epidermidisand Staphylococcus saprophyticus)

Streptococcus agalactiae

Group D streptococci

Viridans group streptococci

Aerobic and facultative Gram-negative microorganisms:

Citrobacter amalonaticus

Citrobacter diversus

Citrobacter freundii

Klebsiella oxytoca

Klebsiella ozaenae

NOTE: Some strains of Enterobacterspecies and Klebsiellaspecies are resistant to nitrofurantoin.

Susceptibility Testing:

For specific information regarding susceptibility test interpretive criteria and associated test methods and quality control standards recognized by FDA for this drug, please see: https://www.fda.gov/STIC.

INDICATIONS AND USAGE

Nitrofurantoin capsules (macrocrystals) are specifically indicated for the treatment of urinary tract infections when due to susceptible strains of Escherichia coli, enterococci, Staphylococcus aureus, and certain susceptible strains of Klebsiellaand Enterobacterspecies.

Nitrofurantoin is not indicated for the treatment of pyelonephritis or perinephric abscesses.

To reduce the development of drug-resistant bacteria and maintain the effectiveness of nitrofurantoin capsules (macrocrystals) and other antibacterial drugs, nnitrofurantoin capsules (macrocrystals) should be used only to treat or prevent infections that are proven or strongly suspected to be caused by susceptible bacteria. When culture and susceptibility information are available, they should be considered in selecting or modifying antibacterial therapy. In the absence of such data, local epidemiology and susceptibility patterns may contribute to the empiric selection of therapy.

Nitrofurantoins lack the broader tissue distribution of other therapeutic agents approved for urinary tract infections. Consequently, many patients who are treated with nitrofurantoin capsules (macrocrystals) are predisposed to persistence or reappearance of bacteriuria. Urine specimens for culture and susceptibility testing should be obtained before and after completion of therapy. If persistence or reappearance of bacteriuria occurs after treatment with nitrofurantoin capsules (macrocrystals), other therapeutic agents with broader tissue distribution should be selected. In considering the use of nitrofurantoin capsules (macrocrystals), lower eradication rates should be balanced against the increased potential for systemic toxicity and for the development of antimicrobial resistance when agents with broader tissue distribution are utilized.

CONTRAINDICATIONS

Anuria, oliguria, or significant impairment of renal function (creatinine clearance under 60 mL per minute or clinically significant elevated serum creatinine) are contraindications. Treatment of this type of patient carries an increased risk of toxicity because of impaired excretion of the drug.

Because of the possibility of hemolytic anemia due to immature erythrocyte enzyme systems (glutathione instability), the drug is contraindicated in pregnant patients at term (38 to 42 weeks’ gestation), during labor and delivery, or when the onset of labor is imminent. For the same reason, the drug is contraindicated in neonates under one month of age.

Nitrofurantoin capsules (macrocrystals) are contraindicated in patients with a previous history of cholestatic jaundice/hepatic dysfunction associated with nitrofurantoin.

Nitrofurantoin capsules (macrocrystals) are also contraindicated in those patients with known hypersensitivity to nitrofurantoin.

WARNINGS

Pulmonary reactions:

ACUTE, SUBACUTE, OR CHRONIC PULMONARY REACTIONS HAVE BEEN OBSERVED IN PATIENTS TREATED WITH NITROFURANTOIN. IF THESE REACTIONS OCCUR, NITROFURANTOIN CAPSULES (MACROCRYSTALS) SHOULD BE DISCONTINUED AND APPROPRIATE MEASURES TAKEN. REPORTS HAVE CITED PULMONARY REACTIONS AS A CONTRIBUTING CAUSE OF DEATH.

CHRONIC PULMONARY REACTIONS (DIFFUSE INTERSTITIAL PNEUMONITIS OR PULMONARY FIBROSIS, OR BOTH) CAN DEVELOP INSIDIOUSLY. THESE REACTIONS OCCUR RARELY AND GENERALLY IN PATIENTS RECEIVING THERAPY FOR SIX MONTHS OR LONGER. CLOSE MONITORING OF THE PULMONARY CONDITION OF PATIENTS RECEIVING LONG-TERM THERAPY IS WARRANTED AND REQUIRES THAT THE BENEFITS OF THERAPY BE WEIGHED AGAINST POTENTIAL RISKS (SEE RESPIRATORY REACTIONS).

Hepatotoxicity:

Hepatic reactions, including hepatitis, cholestatic jaundice, chronic active hepatitis, and hepatic necrosis, occur rarely. Fatalities have been reported. The onset of chronic active hepatitis may be insidious, and patients should be monitored periodically for changes in biochemical tests that would indicate liver injury. If hepatitis occurs, the drug should be withdrawn immediately and appropriate measures should be taken.

Neuropathy:

Peripheral neuropathy, which may become severe or irreversible, has occurred. Fatalities have been reported. Conditions such as renal impairment (creatinine clearance under 60 mL per minute or clinically significant elevated serum creatinine), anemia, diabetes mellitus, electrolyte imbalance, vitamin B deficiency, and debilitating disease may enhance the occurrence of peripheral neuropathy. Patients receiving long-term therapy should be monitored periodically for changes in renal function.

Optic neuritis has been reported rarely in postmarketing experience with nitrofurantoin formulations.

Hemolytic anemia:

Cases of hemolytic anemia of the primaquine-sensitivity type have been induced by nitrofurantoin. Hemolysis appears to be linked to a glucose-6-phosphate dehydrogenase deficiency in the red blood cells of the affected patients. This deficiency is found in 10 percent of Blacks and a small percentage of ethnic groups of Mediterranean and Near-Eastern origin. Hemolysis is an indication for discontinuing nitrofurantoin capsules (macrocrystals); hemolysis ceases when the drug is withdrawn.

Clostridium difficile-associated diarrhea:

Clostridium difficileassociated diarrhea (CDAD) has been reported with use of nearly all antibacterial agents, including nitrofurantoin, and may range in severity from mild diarrhea to fatal colitis. Treatment with antibacterial agents alters the normal flora of the colon leading to overgrowth of C. difficile.

C. difficileproduces toxins A and B which contribute to the development of CDAD. Hypertoxin producing strains of C. difficilecause increased morbidity and mortality, as these infections can be refractory to antimicrobial therapy and may require colectomy. CDAD must be considered in all patients who present with diarrhea following antibiotic use. Careful medical history is necessary since CDAD has been reported to occur over two months after the administration of antibacterial agents.

If CDAD is suspected or confirmed, ongoing antibiotic use not directed against C. difficilemay need to be discontinued. Appropriate fluid and electrolyte management, protein supplementation, antibiotic treatment of C. difficile, and surgical evaluation should be instituted as clinically indicated.

PRECAUTIONS

Information for Patients

Patients should be advised to take nitrofurantoin capsules (macrocrystals) with food to further enhance tolerance and improve drug absorption. Patients should be instructed to complete the full course of therapy; however, they should be advised to contact their physician if any unusual symptoms occur during therapy.

Many patients who cannot tolerate microcrystalline nitrofurantoin are able to take nitrofurantoin capsules (macrocrystals) without nausea.

Patients should be advised not to use antacid preparations containing magnesium trisilicate while taking nitrofurantoin capsules (macrocrystals).

Patients should be counseled that antibacterial drugs including nitrofurantoin capsules (macrocrystals) should only be used to treat bacterial infections. They do not treat viral infections (e.g., the common cold). When nitrofurantoin capsules (macrocrystals) is prescribed to treat a bacterial infection, patients should be told that although it is common to feel better early in the course of therapy, the medication should be taken exactly as directed. Skipping doses or not completing the full course of therapy may (1) decrease the effectiveness of the immediate treatment and (2) increase the likelihood that bacteria will develop resistance and will not be treatable by nitrofurantoin capsules (macrocrystals) or other antibacterial drugs in the future.

Diarrhea is a common problem caused by antibiotics which usually ends when the antibiotic is discontinued. Sometimes after starting treatment with antibiotics, patients can develop watery and bloody stools (with or without stomach cramps and fever) even as late as two or more months after having taken the last dose of the antibiotic. If this occurs, patients should contact their physician as soon as possible.

General:Prescribing nitrofurantoin capsules (macrocrystals) in the absence of a proven or strongly suspected bacterial infection or a prophylactic indication is unlikely to provide benefit to the patient and increases the risk of the development of drug-resistant bacteria.

Drug Interactions

Antacids containing magnesium trisilicate, when administered concomitantly with nitrofurantoin, reduce both the rate and extent of absorption. The mechanism for this interaction probably is adsorption of nitrofurantoin onto the surface of magnesium trisilicate.

Uricosuric drugs, such as probenecid and sulfinpyrazone, can inhibit renal tubular secretion of nitrofurantoin. The resulting increase in nitrofurantoin serum levels may increase toxicity, and the decreased urinary levels could lessen its efficacy as a urinary tract antibacterial.

Drug/Laboratory Test Interactions:

As a result of the presence of nitrofurantoin, a false-positive reaction for glucose in the urine may occur. This has been observed with Benedict's and Fehling's solutions but not with the glucose enzymatic test.

Carcinogenesis, Mutagenesis, Impairment of Fertility:

Nitrofurantoin was not carcinogenic when fed to female Holtzman rats for 44.5 weeks or to female Sprague-Dawley rats for 75 weeks. Two chronic rodent bioassays utilizing male and female Sprague-Dawley rats and two chronic bioassays in Swiss mice and in BDF1mice revealed no evidence of carcinogenicity.

Nitrofurantoin presented evidence of carcinogenic activity in female B6C3F1mice as shown by increased incidences of tubular adenomas, benign mixed tumors, and granulosa cell tumors of the ovary. In male F344/N rats, there were increased incidences of uncommon kidney tubular cell neoplasms, osteosarcomas of the bone, and neoplasms of the subcutaneous tissue. In one study involving subcutaneous administration of 75 mg/kg nitrofurantoin to pregnant female mice, lung papillary adenomas of unknown significance were observed in the F1 generation.

Nitrofurantoin has been shown to induce point mutations in certain strains of Salmonella typhimuriumand forward mutations in L5178Y mouse lymphoma cells. Nitrofurantoin induced increased numbers of sister chromatid exchanges and chromosomal aberrations in Chinese hamster ovary cells but not in human cells in culture. Results of the sex-linked recessive lethal assay in Drosophila were negative after administration of nitrofurantoin by feeding or by injection. Nitrofurantoin did not induce heritable mutation in the rodent models examined.

The significance of the carcinogenicity and mutagenicity findings relative to the therapeutic use of nitrofurantoin in humans is unknown.

The administration of high doses of nitrofurantoin to rats causes temporary spermatogenic arrest; this is reversible on discontinuing the drug. Doses of 10 mg/kg/day or greater in healthy human males may, in certain unpredictable instances, produce a slight to moderate spermatogenic arrest with a decrease in sperm count.

Pregnancy

Teratogenic effects:

Several reproduction studies have been performed in rabbits and rats at doses up to 6 times the human dose and have revealed no evidence of impaired fertility or harm to the fetus due to nitrofurantoin. In a single published study conducted in mice at 68 times the human dose (based on mg/kg administered to the dam), growth retardation and a low incidence of minor and common malformations were observed. However, at 25 times the human dose, fetal malformations were not observed; the relevance of these findings to humans is uncertain. There are, however, no adequate and well-controlled studies in pregnant women. Because animal reproduction studies are not always predictive of human response, this drug should be used during pregnancy only if clearly needed.

Non-teratogenic effects:

Nitrofurantoin has been shown in one published transplacental carcinogenicity study to induce lung papillary adenomas in the F1 generation mice at doses 19 times the human dose on a mg/kg basis. The relationship of this finding to potential human carcinogenesis is presently unknown. Because of the uncertainty regarding the human implications of these animal data, this drug should be used during pregnancy only if clearly needed.

Labor and Delivery

See CONTRAINDICATIONS.

Nursing Mothers

Nitrofurantoin has been detected in human breast milk in trace amounts. Because of the potential for serious adverse reactions from nitrofurantoin in nursing infants under one month of age, a decision should be made whether to discontinue nursing or to discontinue the drug, taking into account the importance of the drug to the mother (see CONTRAINDICATIONS).

Pediatric Use

Nitrofurantoin capsules (macrocrystals) are contraindicated in infants below the age of one month (see CONTRAINDICATIONS).

Geriatric Use

Clinical studies of nitrofurantoin macrocrystals capsules did not include sufficient numbers of subjects aged 65 and over to determine whether they respond differently from younger subjects. Other reported clinical experience has not identified differences in responses between the elderly and younger patients. Spontaneous reports suggest a higher proportion of pulmonary reactions, including fatalities, in elderly patients; these differences appear to be related to the higher proportion of elderly patients receiving long-term nitrofurantoin therapy. As in younger patients, chronic pulmonary reactions generally are observed in patients receiving therapy for six months or longer (see WARNINGS). Spontaneous reports also suggest an increased proportion of severe hepatic reactions, including fatalities, in elderly patients (see WARNINGS).

In general, the greater frequency of decreased hepatic, renal, or cardiac function, and of concomitant disease or other drug therapy should be considered when prescribing nitrofurantoin capsules (macrocrystals). This drug is known to be substantially excreted by the kidney, and the risk of toxic reactions to this drug may be greater in patients with impaired renal function. Anuria, oliguria, or significant impairment of renal function (creatinine clearance under 60 mL per minute or clinically significant elevated serum creatinine) are contraindications (see CONTRAINDICATIONS). Because elderly patients are more likely to have decreased renal function, care should be taken in dose selection, and it may be useful to monitor renal function.

ADVERSE REACTIONS

Respiratory:

CHRONIC, SUBACUTE, OR ACUTE PULMONARY HYPERSENSITIVITY REACTIONS MAY OCCUR.

CHRONIC PULMONARY REACTIONS OCCUR GENERALLY IN PATIENTS WHO HAVE RECEIVED CONTINUOUS TREATMENT FOR SIX MONTHS OR LONGER. MALAISE, DYSPNEA ON EXERTION, COUGH, AND ALTERED PULMONARY FUNCTION ARE COMMON MANIFESTATIONS WHICH CAN OCCUR INSIDIOUSLY. RADIOLOGIC AND HISTOLOGIC FINDINGS OF DIFFUSE INTERSTITIAL PNEUMONITIS OR FIBROSIS, OR BOTH, ARE ALSO COMMON MANIFESTATIONS OF THE CHRONIC PULMONARY REACTION. FEVER IS RARELY PROMINENT.

THE SEVERITY OF CHRONIC PULMONARY REACTIONS AND THEIR DEGREE OF RESOLUTION APPEAR TO BE RELATED TO THE DURATION OF THERAPY AFTER THE FIRST CLINICAL SIGNS APPEAR. PULMONARY FUNCTION MAY BE IMPAIRED PERMANENTLY, EVEN AFTER CESSATION OF THERAPY. THE RISK IS GREATER WHEN CHRONIC PULMONARY REACTIONS ARE NOT RECOGNIZED EARLY.

In subacute pulmonary reactions, fever and eosinophilia occur less often than in the acute form. Upon cessation of therapy, recovery may require several months. If the symptoms are not recognized as being drug-related and nitrofurantoin therapy is not stopped, the symptoms may become more severe.

Acute pulmonary reactions are commonly manifested by fever, chills, cough, chest pain, dyspnea, pulmonary infiltration with consolidation or pleural effusion on x-ray, and eosinophilia. Acute reactions usually occur within the first week of treatment and are reversible with cessation of therapy. Resolution often is dramatic (see WARNINGS).

Changes in EKG (e.g., non-specific ST/T wave changes, bundle branch block) have been reported in association with pulmonary reactions.

Cyanosis has been reported rarely.

Hepatic:Hepatic reactions, including hepatitis, cholestatic jaundice, chronic active hepatitis, and hepatic necrosis, occur rarely (see WARNINGS).

Neurologic: Peripheral neuropathy, which may become severe or irreversible, has occurred. Fatalities have been reported. Conditions such as renal impairment (creatinine clearance under 60 mL per minute or clinically significant elevated serum creatinine), anemia, diabetes mellitus, electrolyte imbalance, vitamin B deficiency, and debilitating diseases may increase the possibility of peripheral neuropathy (see WARNINGS).

Asthenia, vertigo, nystagmus, dizziness, headache, and drowsiness also have been reported with the use of nitrofurantoin.

Benign intracranial hypertension (pseudotumor cerebri), confusion, depression, optic neuritis, and psychotic reactions have been reported rarely. Bulging fontanels, as a sign of benign intracranial hypertension in infants, have been reported rarely.

Dermatologic:Exfoliative dermatitis and erythema multiforme (including Stevens-Johnson syndrome) have been reported rarely. Transient alopecia also has been reported.

Allergic:A lupus-like syndrome associated with pulmonary reactions to nitrofurantoin has been reported. Also, angioedema; maculopapular, erythematous, or eczematous eruptions; pruritus; urticaria; anaphylaxis; arthralgia; myalgia; drug fever; chills; and vasculitis (sometimes associated with pulmonary reactions) have been reported. Hypersensitivity reactions represent the most frequent spontaneously-reported adverse events in worldwide postmarketing experience with nitrofurantoin formulations.

Gastrointestinal:Nausea, emesis, and anorexia occur most often. Abdominal pain and diarrhea are less common gastrointestinal reactions. These dose-related reactions can be minimized by reduction of dosage. Sialadenitis and pancreatitis have been reported. There have been sporadic reports of pseudomembranous colitis with the use of nitrofurantoin. The onset of pseudomembranous colitis symptoms may occur during or after antimicrobial treatment (see WARNINGS).

Hematologic:Cyanosis secondary to methemoglobinemia has been reported rarely.

Miscellaneous:As with other antimicrobial agents, superinfections caused by resistant organisms, e.g., Pseudomonasspecies or Candidaspecies, can occur.

Laboratory Adverse Events:The following laboratory adverse events have been reported with the use of nitrofurantoin: increased AST (SGOT), increased ALT (SGPT), decreased hemoglobin, increased serum phosphorus, eosinophilia, glucose-6-phosphate dehydrogenase deficiency anemia (see WARNINGS), agranulocytosis, leukopenia, granulocytopenia, hemolytic anemia, thrombocytopenia, megaloblastic anemia. In most cases, these hematologic abnormalities resolved following cessation of therapy. Aplastic anemia has been reported rarely.

To report SUSPECTED ADVERSE REACTIONS, contact Alvogen, Inc. at 1-866-770-3024 or FDA at 1-800-FDA-1088 or www.fda.gov/medwatch.

OVERDOSAGE

Occasional incidents of acute overdosage of nitrofurantoin capsules (macrocrystals) have not resulted in any specific symptoms other than vomiting. Induction of emesis is recommended. There is no specific antidote, but a high fluid intake should be maintained to promote urinary excretion of the drug. It is dialyzable.

DOSAGE AND ADMINISTRATION

Nitrofurantoin capsules (macrocrystals) should be given with food to improve drug absorption and, in some patients, tolerance.

Adults:50 mg to 100 mg four times a day -- the lower dosage level is recommended for uncomplicated urinary tract infections.

Pediatric Patients:5 mg/kg to 7 mg/kg of body weight per 24 hours, given in four divided doses (contraindicated under one month of age).

Therapy should be continued for one week or for at least 3 days after sterility of the urine is obtained. Continued infection indicates the need for reevaluation.

For long-term suppressive therapy in adults, a reduction of dosage to 50 mg to 100 mg at bedtime may be adequate. For long-term suppressive therapy in pediatric patients, doses as low as 1 mg/kg per 24 hours, given in a single dose or in two divided doses, may be adequate. SEE WARNINGSSECTION REGARDING RISKS ASSOCIATED WITH LONG-TERM THERAPY.

HOW SUPPLIED

Nitrofurantoin capsules (macrocrystals) are available as follows:

100 mgopaque, yellow capsule imprinted with “MACRODANTIN 100 mg” and “52427-288”.

NDC 51655-948-53 bottle of 10

NDC 51655-948-84 bottle of 14

NDC 51655-948-20 bottle of 20

NDC 51655-948-29 bottle of 28

Store at controlled room temperature 20ºC to 25ºC (68ºF to 77ºF) [See USP].

Dispense in a tight, light-resistant container as defined in the USP using a child-resistant closure.

Distributed by: Alvogen, Inc.
Morristown, NJ 07960 USA

Rev: 06/2023 PI306-08

Principal Display Panel

NDC: 51655-948-20